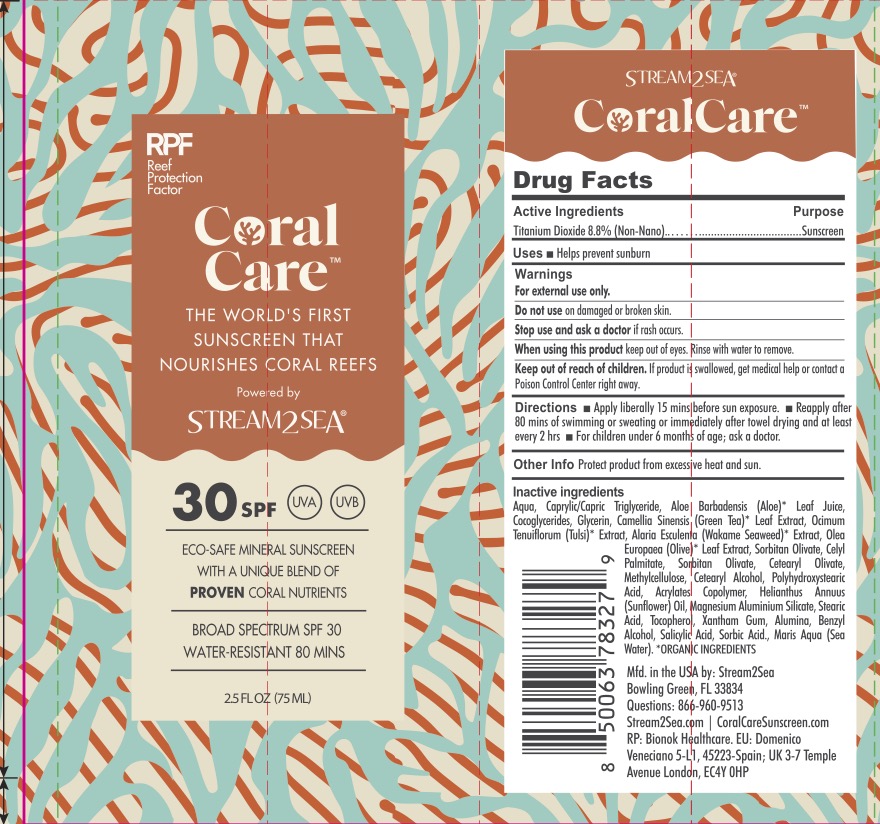 DRUG LABEL: Coral Care SPF 30 Sunscreen
NDC: 69555-032 | Form: LOTION
Manufacturer: Stream2Sea
Category: otc | Type: HUMAN OTC DRUG LABEL
Date: 20241119

ACTIVE INGREDIENTS: TITANIUM DIOXIDE 8.8 g/100 mL
INACTIVE INGREDIENTS: WATER; GREEN TEA LEAF; STEARIC ACID; CETEARYL ALCOHOL; SALICYLIC ACID; MEDIUM-CHAIN TRIGLYCERIDES; ALOE VERA LEAF; MAGNESIUM ALUMINUM SILICATE; XANTHAN GUM; ALUMINA; COCOGLYCERIDES; GLYCERIN; ALARIA ESCULENTA; SORBIC ACID; SODIUM CHLORIDE; CETEARYL OLIVATE; CETYL PALMITATE; POLYHYDROXYSTEARIC ACID (2300 MW); BUTYL ACRYLATE/METHYL METHACRYLATE/METHACRYLIC ACID COPOLYMER (18000 MW); METHYLCELLULOSE; HOLY BASIL LEAF; SUNFLOWER OIL; BENZYL ALCOHOL; SORBITAN OLIVATE; OLEA EUROPAEA LEAF; TOCOPHEROL

Coral Care SPF 30

ACTIVE INGREDIENT

Titanium Dioxide 8.8%

PURPOSE

Sunscreen

INDICATIONS AND USAGE

Helps prevent sunburn.

WARNINGS

For external use only.

Do not use on damaged or broken skin.

Stop use and ask a doctor if rash occurs.

When using this product keep out of eyes. Rinse with water to remove.

KEEP OUT OF REACH OF CHILDREN

If product is swallowed, get medical help or contact a Poison Control Center right away.

DOSAGE AND ADMINISTRATION

Directions: apply liberally 15 minutes before sun exposure. Reapply after 80 minutes of swimming or sweating or immediately after towel drying and at lease every 2 hours. For children under 6 months of age: ask a doctor.

INACTIVE INGREDIENT

Water/Aqua, Caprylic/Capric Triglyceride, Aloe Barbadensis (Aloe)* Leaf Juice, Cocoglycerides, Glycerin, Camellia Sinensis (Green Tea)* Leaf Extract, Ocimum Tenuiflorum (Tulsi)* Extract, Alaria Esculenta (Wakame Seaweed)* Extract, Olea Europaea (Olive)* Leaf Extract, Sorbitan Olivate, Cetyl Palmitate, Cetearyl Olivate, Methylcellulose, Cetearyl Alcohol, Polyhydroxystearic Acid, Acrylates Copolymer, Helianthus Annuus (Sunflower) Oil, Magnesium Aluminum Silicate, Stearic Acid, Tocopherol, Xanthan Gum, Alumina, Benzyl Alcohol, Salicylic Acid, Sorbic Acid, Maris Aqua (Sea Water).

*Organic Ingredients